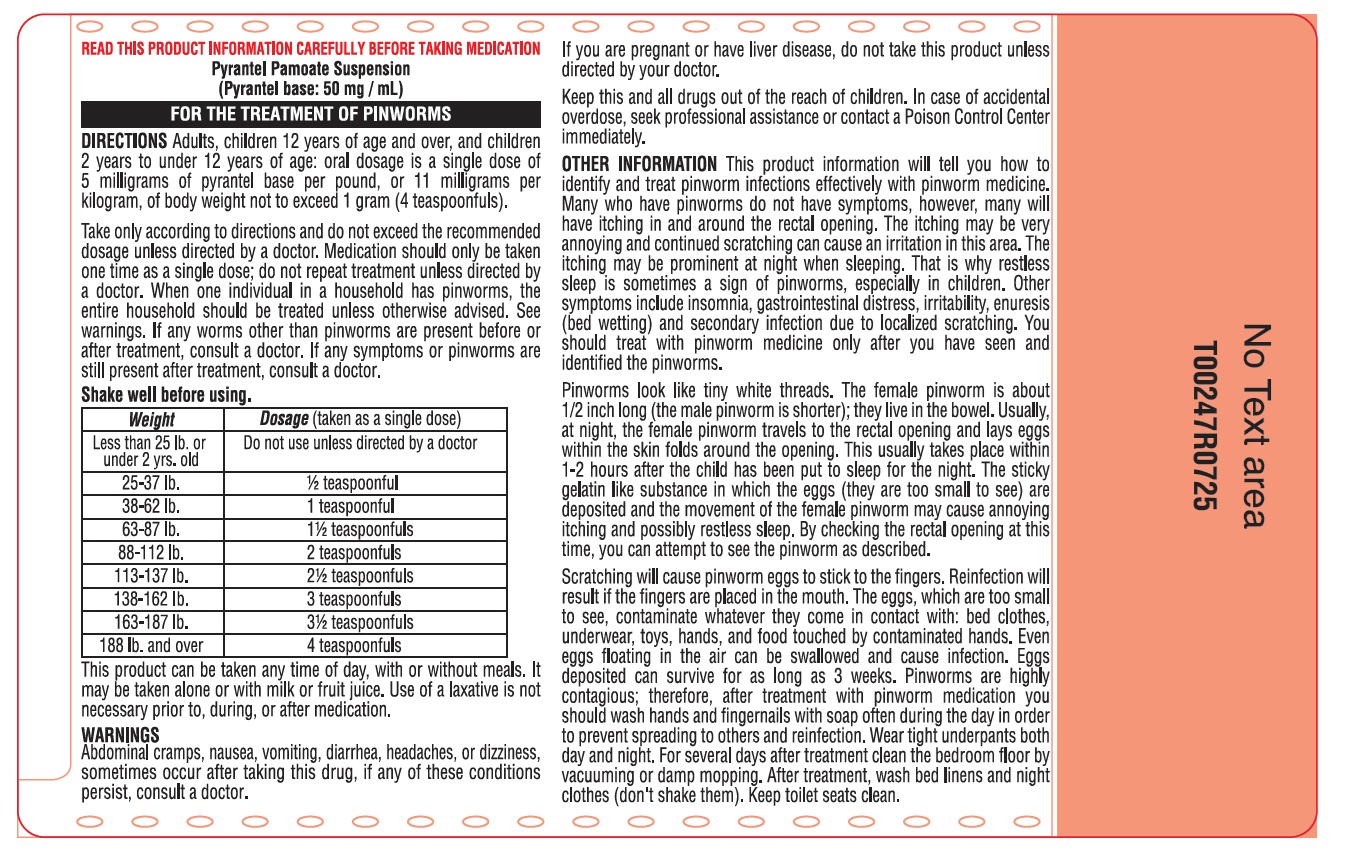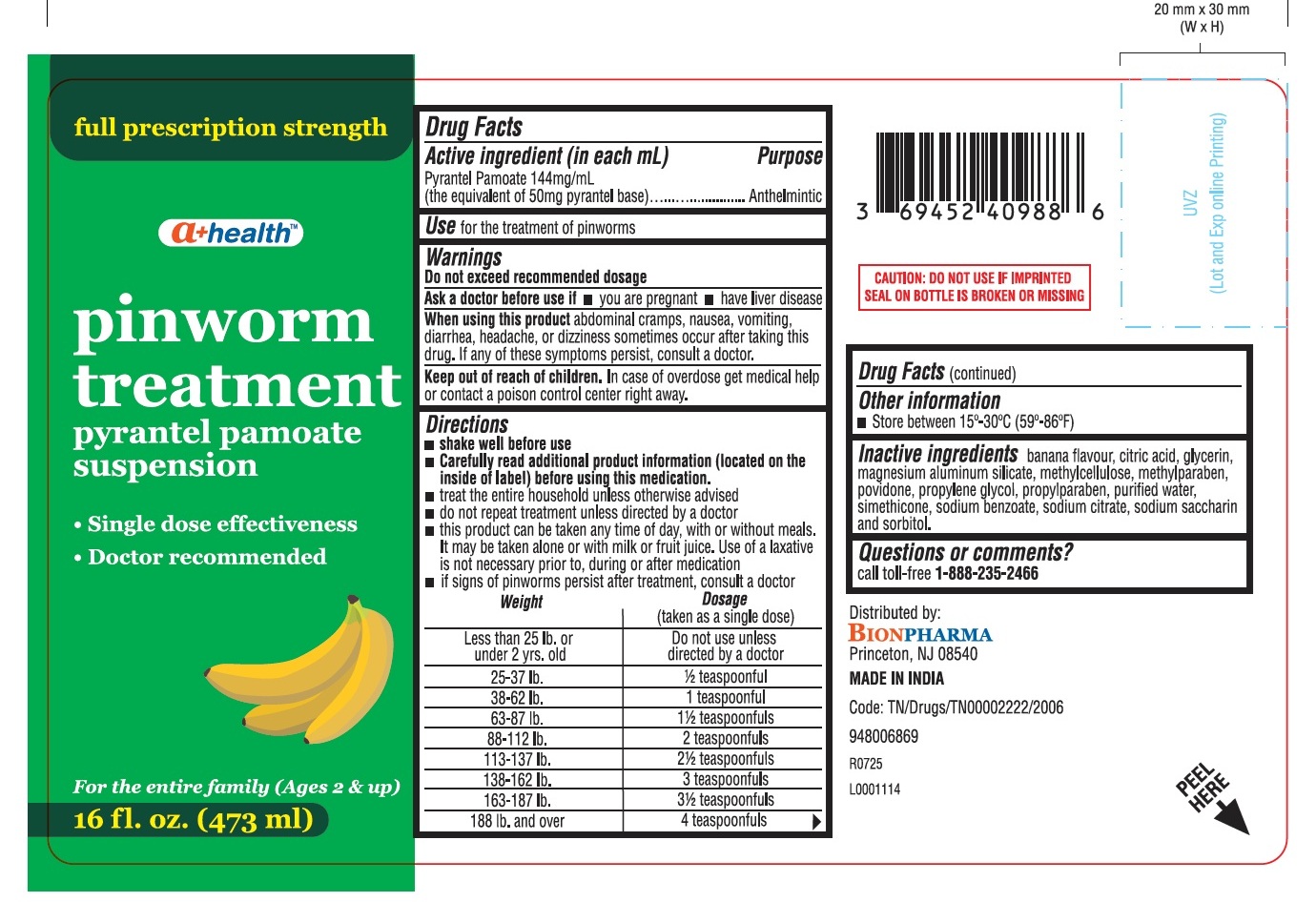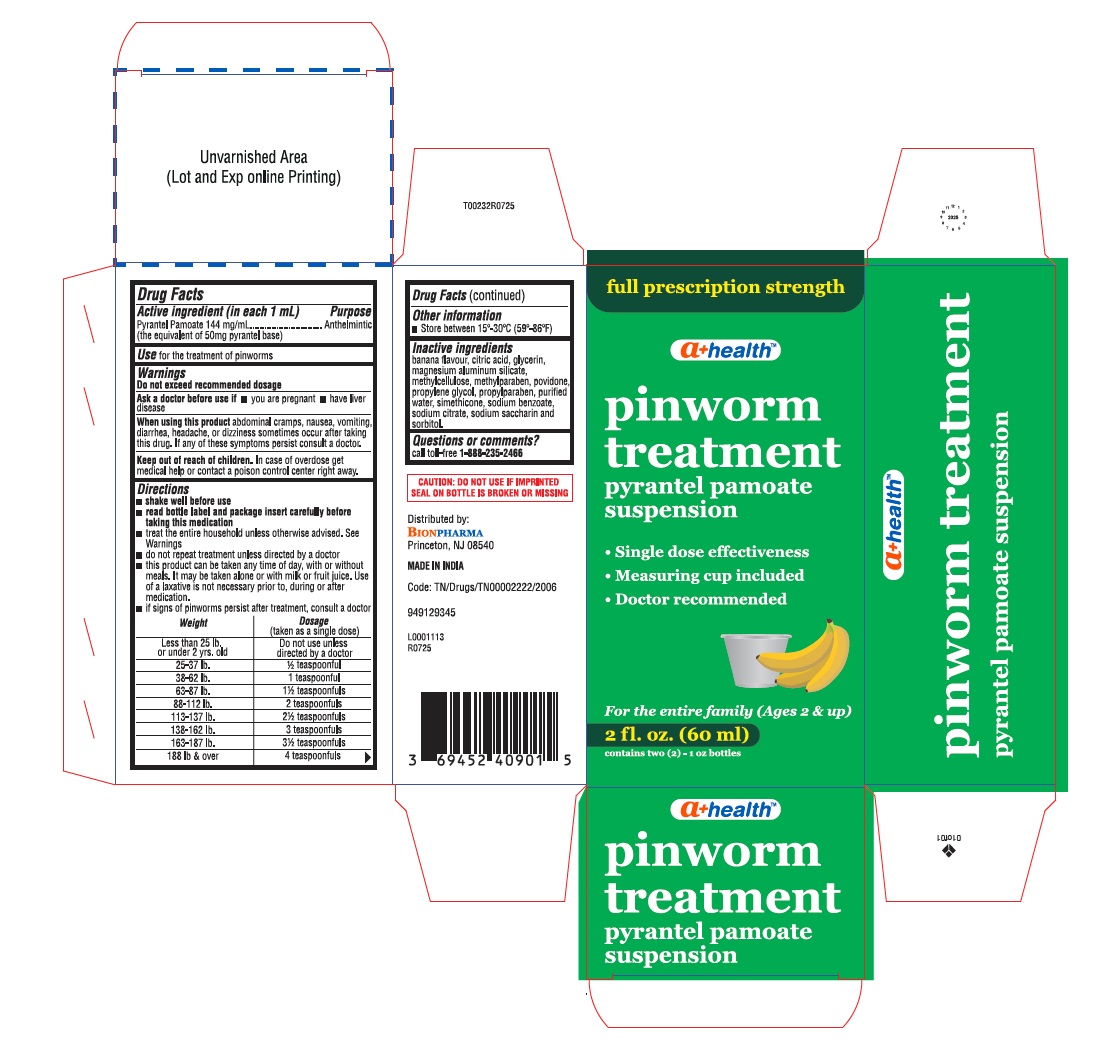 DRUG LABEL: pinworm treatment
NDC: 69452-515 | Form: SUSPENSION
Manufacturer: BIONPHARMA INC.
Category: otc | Type: HUMAN OTC DRUG LABEL
Date: 20260123

ACTIVE INGREDIENTS: PYRANTEL PAMOATE 144 mg/1 mL
INACTIVE INGREDIENTS: CITRIC ACID; GLYCERIN; MAGNESIUM ALUMINUM SILICATE; METHYLCELLULOSE; POVIDONE; DIMETHICONE; SODIUM BENZOATE; SODIUM CITRATE; SACCHARIN SODIUM; SORBITOL; WATER; PROPYLPARABEN; PROPYLENE GLYCOL; METHYLPARABEN

pinworm treatment-a+ health

Active ingredient (in each mL)

Pyrantel Pamoate 144mg/mL

(the equivalent of 50mg pyrantel base)

Purpose

Anthelimintic

Use

for the treatment of pinworns

Warnings

Do not exceed recommended dosage

Ask a doctor before use if

■ you are pregnant ■ have liver disease

When using this product

abdominal cramps, nausea, vomiting, diarrhea, headache, or dizziness sometimes occur after taking this drug. If any of these symptoms persist, consult a doctor.

Keep out of reach of children.

In case of overdose get medical help or contact a poison control center right away.

Directions

■ shake well before use

■ read bottle label and package insert carefully before taking this medication

■ treat the entire household unless otherwise advised. See Warnings

■ do not repeat treatment unless directed by a doctor

■ this product can be taken any time of day, with or without meals. It may be taken alone or with milk or fruit juice. Use of a laxative is not necessary prior to, during or after medication

■ if signs of pinworms persist after treatment, consult a doctor

Weight | Dosage; (taken as a single dose)
Less than 25 lb. or under 2 yrs.old | Do not use unless directed by a doctor
25-37 lb. | 1/2 teaspoonful
38-62 lb. | 1 teaspoonful
63-87 lb. | 1 1/2 teaspoonfuls
88-112 lb. | 2 teaspoonfuls
113-137 lb. | 2 1/2 teaspoonfuls
138-162 lb. | 3 teaspoonfuls
163-187 lb. | 3 1/2 teaspoonfuls
188 lb. and over | 4 teaspoonfuls

Other information

■ Store between 15°C-30°C (59°- 86°F)

Inactive ingredients

banana flavor, citric acid, gylcerin, lecithin, magnesium aluminum silicate, methylcellulose, methylparaben, povidone, propylene glycol, propylparaben, purified water, simethicone, sodium benzoate, sodium citrate, sodium saccharin and sorbitol.

Questions or comments?

call toll-free 1-888-235-2466

CAUTION: DO NOT USE IF IMPRINTED SEAL ON BOTTLE IS BROKEN OR MISSING

Distributed by:

BIONPHARMA

Princeton, NJ 08540

MADE IN INDIA

Code: TN/Drugs/TN00002222/2006

949129345

L0001113

R0725

PATIENT INFORMATION

READ THIS INSERT CAREFULLY BEFORE TAKING MEDICATION

PINWORM MEDICINE

Pyrantel Pamoate 144 mg/mL
(the equivalent of 50 mg Pyrantel base per mL)

FOR THE TREATMENT OF PINWORMS

DIRECTIONS

Adults, children 12 years of age and over, and children 2 years to under 12 years of age: oral dosage is a single dose of 5 milligrams of pyrantel base per pound, or 11 milligrams per kilogram, of body weight not to exceed 1 gram.

Take only according to directions and do not exceed the recommended dosage unless directed by a doctor. Medication should only be taken one time as a single dose; do not repeat treatment unless directed by a doctor. When one individual in a household has pinworms, the entire household should be treated unless otherwise advised. See warnings. If any worms other than pinworms are present before or after treatment, consult a doctor. If any symptoms or pinworms are still present after treatment, consult a doctor.

Shake well before using.

Weight | Dosage (taken as a single dose)
Less than 25 pounds or under 2 years old | consult a doctor
25 to 37 pounds | ½ teaspoonful
38 to 62 pounds | 1 teaspoonful
63 to 87 pounds | 1½ teaspoonfuls
88 to 112 pounds | 2 teaspoonfuls
113 to 137 pounds | 2½ teaspoonfuls
138 to 162 pounds | 3 teaspoonfuls
163 to 187 pounds | 3½ teaspoonfuls
188 pounds and over | 4 teaspoonfuls

This product can be taken any time of day, with or without meals. It may be taken alone or with milk or fruit juice. Use of a laxative is not necessary prior to, during, or after medication.

WARNINGS
Abdominal cramps, nausea, vomiting, diarrhea, headaches, or dizziness, sometimes occur after taking this drug, if any of these conditions persist consult a doctor.

If you are pregnant or have Liver disease, do not take this product unless directed by your doctor.

Keep this and all drugs out of the reach of children. In case of accidental overdose, seek professional assistance or contact a Poison Control Center immediately.

OTHER INFORMATION
This brochure will tell you how to identify and treat pinworm infections effectively with pinworm medicine. Many who have pinworms do not have symptoms, however, many will have itching in and around the rectal opening. The itching may be very annoying and continued scratching can cause an irritation in this area. The itching may be prominent at night when sleeping. That is why restless sleep is sometimes a sign of pinworms, especially in children. Other symptoms include insomnia, gastrointestinal distress, irritability, enuresis (bed wetting) and secondary infection due to localized scratching. You should treat with pinworm medicine only after you have seen and identified the pinworms.

Pinworms look like tiny white threads. The female pinworm is about 1/2 inch long (the male pinworm is shorter); they live in the bowel. Usually, at night, the female pinworm travels to the rectal opening and lays eggs within the skin folds around the opening. This usually takes place within 1-2 hours after the child has been put to sleep for the night. The sticky gelatin like substance in which the eggs (they are too small to see) are deposited and the movement of the female pinworm may cause annoying itching and possibly restless sleep. By checking the rectal opening at this time, you can attempt to see the pinworm as described.

Scratching will cause pinworm eggs to stick to the fingers. Reinfection will result if the fingers are placed in the mouth. The eggs, which are too small to see, contaminate whatever they come in contact with: bed clothes, underwear, toys, hands, and food touched by contaminated hands. Even eggs floating in the air can be swallowed and cause infection. Eggs deposited can survive for as long as 3 weeks. Pinworms are highly contagious; therefore, after treatment with pinworm medication you should wash hands and fingernails with soap often during the day in order to prevent spreading to others and reinfection. Wear tight underpants
both day and night. For several days after treatment clean the bedroom floor by vacuuming or damp mopping. After treatment, wash bed linens and night clothes (don't shake them). Keep toilet seats clean.

Distributed by: Bionpharma Inc.

Princeton, NJ 08540

MADE IN INDIA
948026846

L0000896
R0924

carton label 2oz

full prescription strength

a+ healthTM

pinworm

treatment

pyrantel pamoate

suspension

- Single dose effectiveness
- Measuring cup included
- Doctor recommended

For the entire family (Ages 2 & up)

2 fl. oz. (60 ml)

contains two (2)-1oz bottles

bottle label 16oz

full prescription strength

a+ healthTM

pinworm

treatment

pyrantel pamoate

suspension

- Single dose effectiveness
- Doctor recommended

For the entire family (Ages 2 & up)

16 fl. oz. (473 ml)